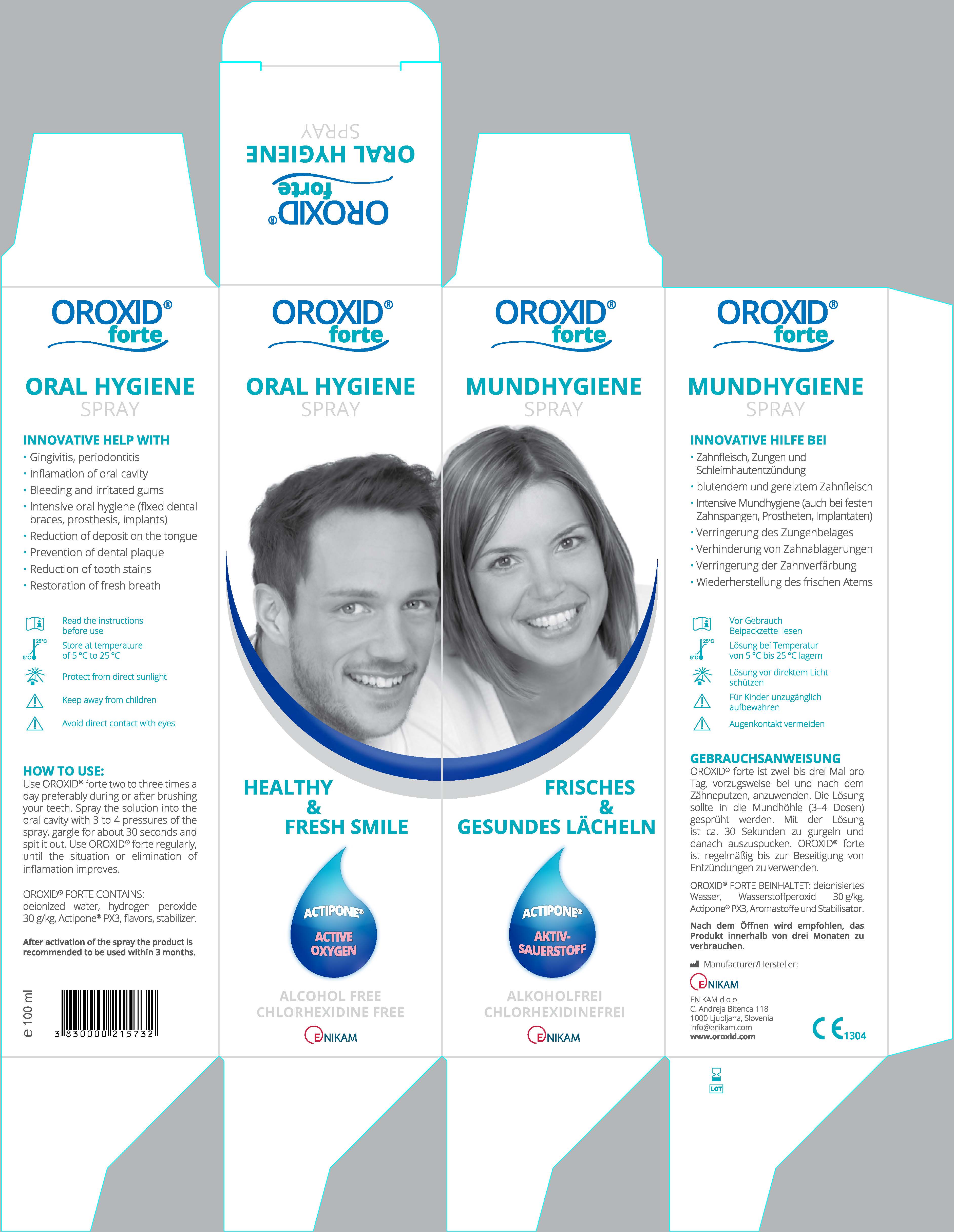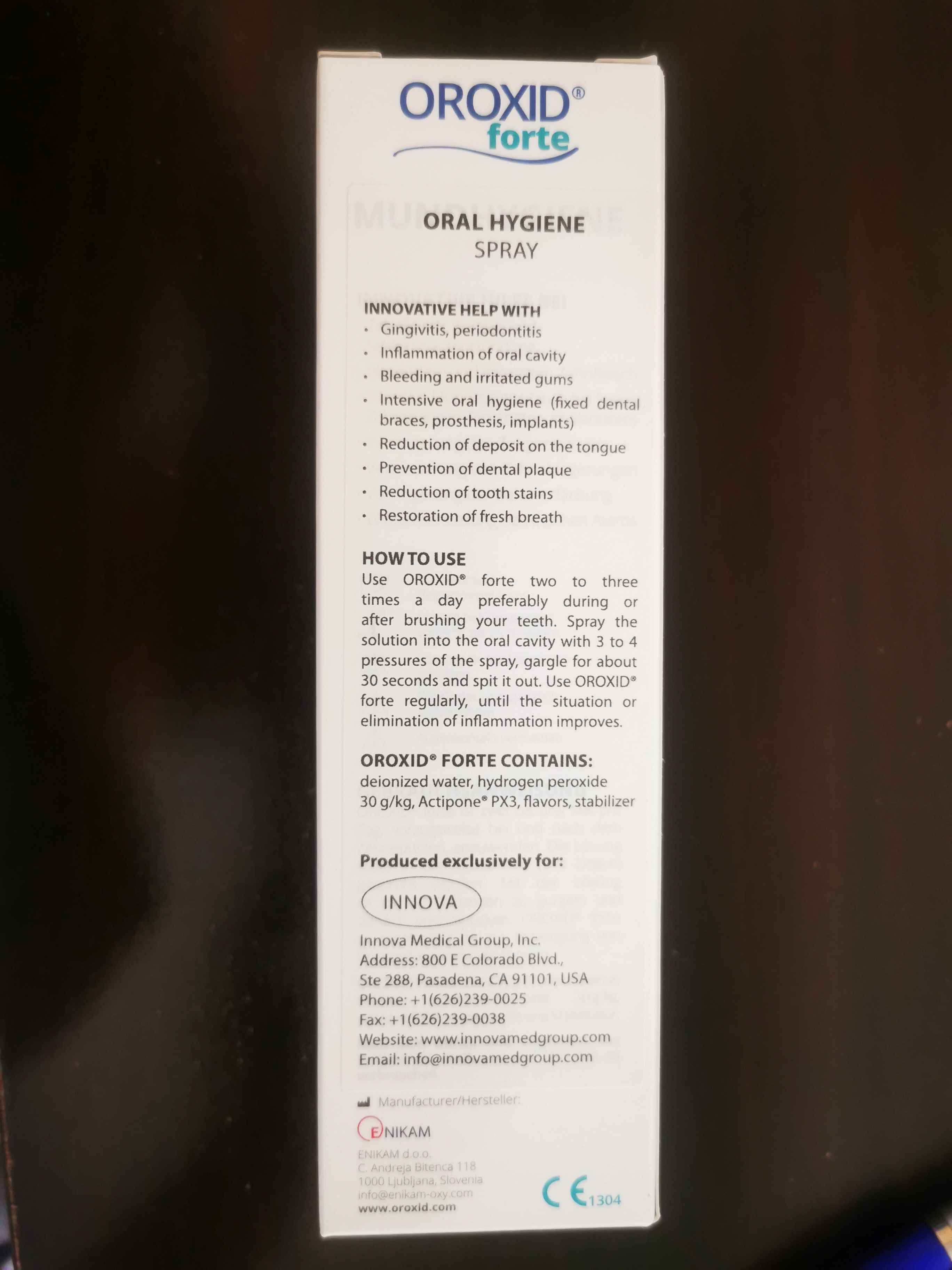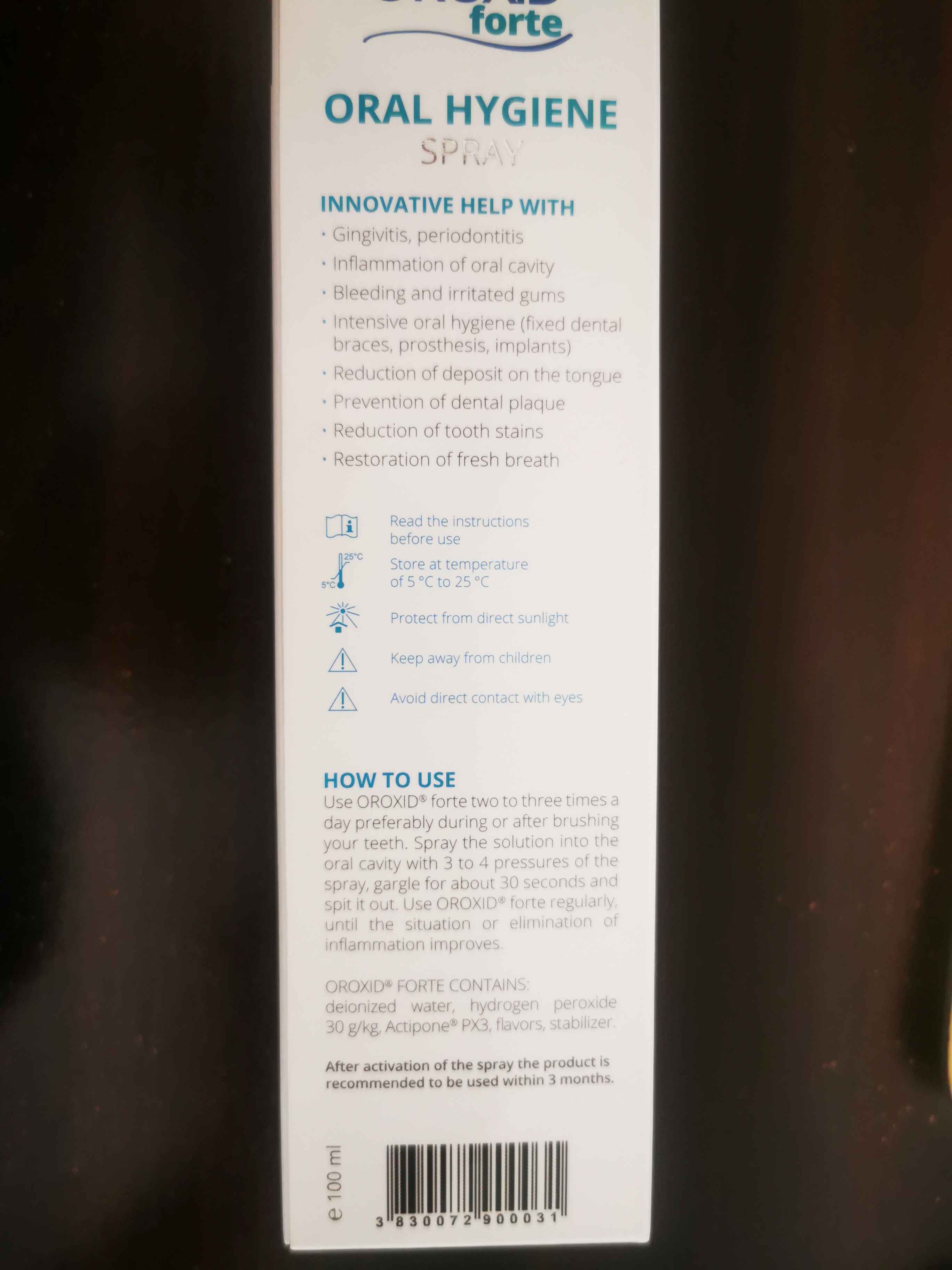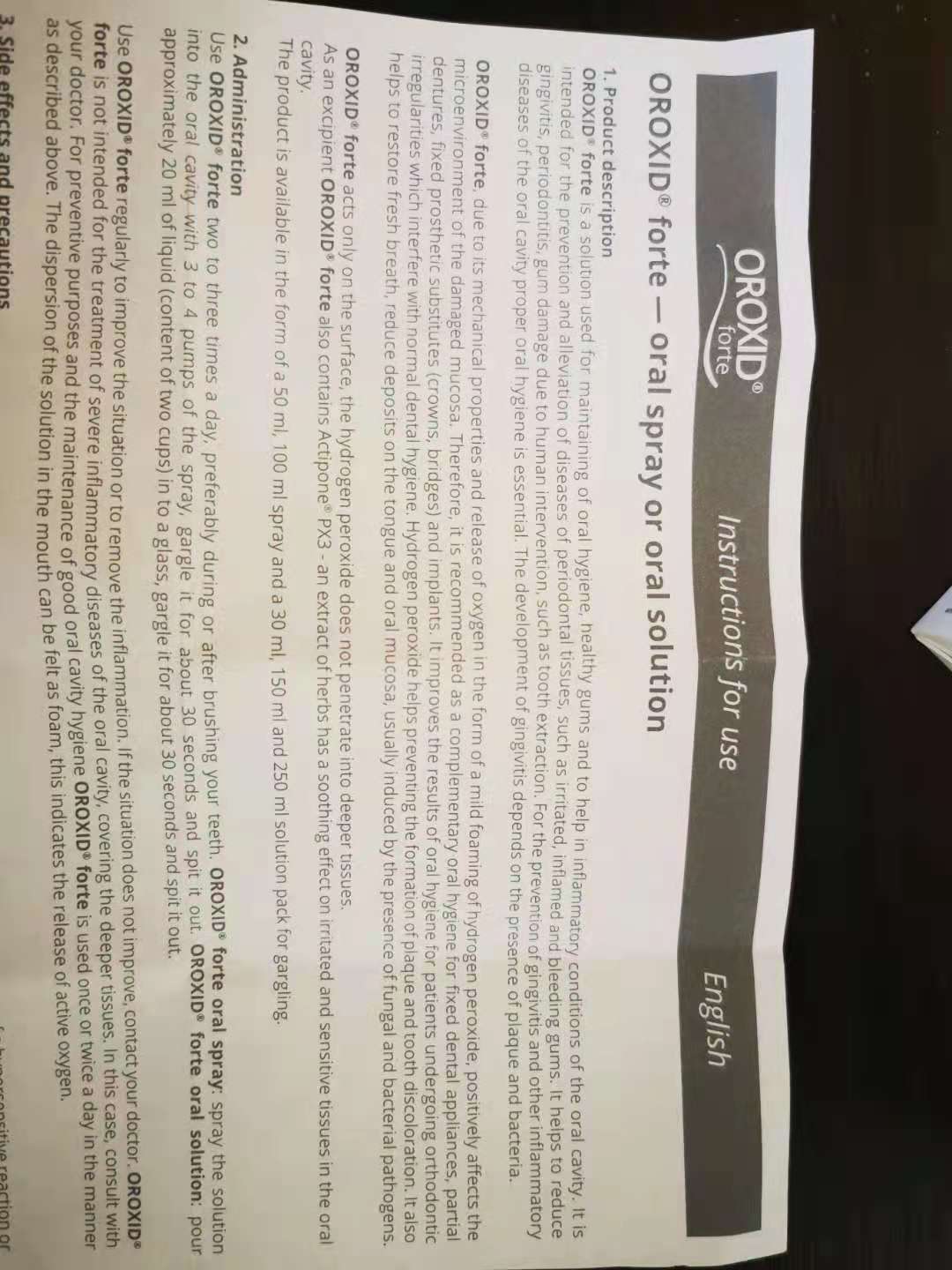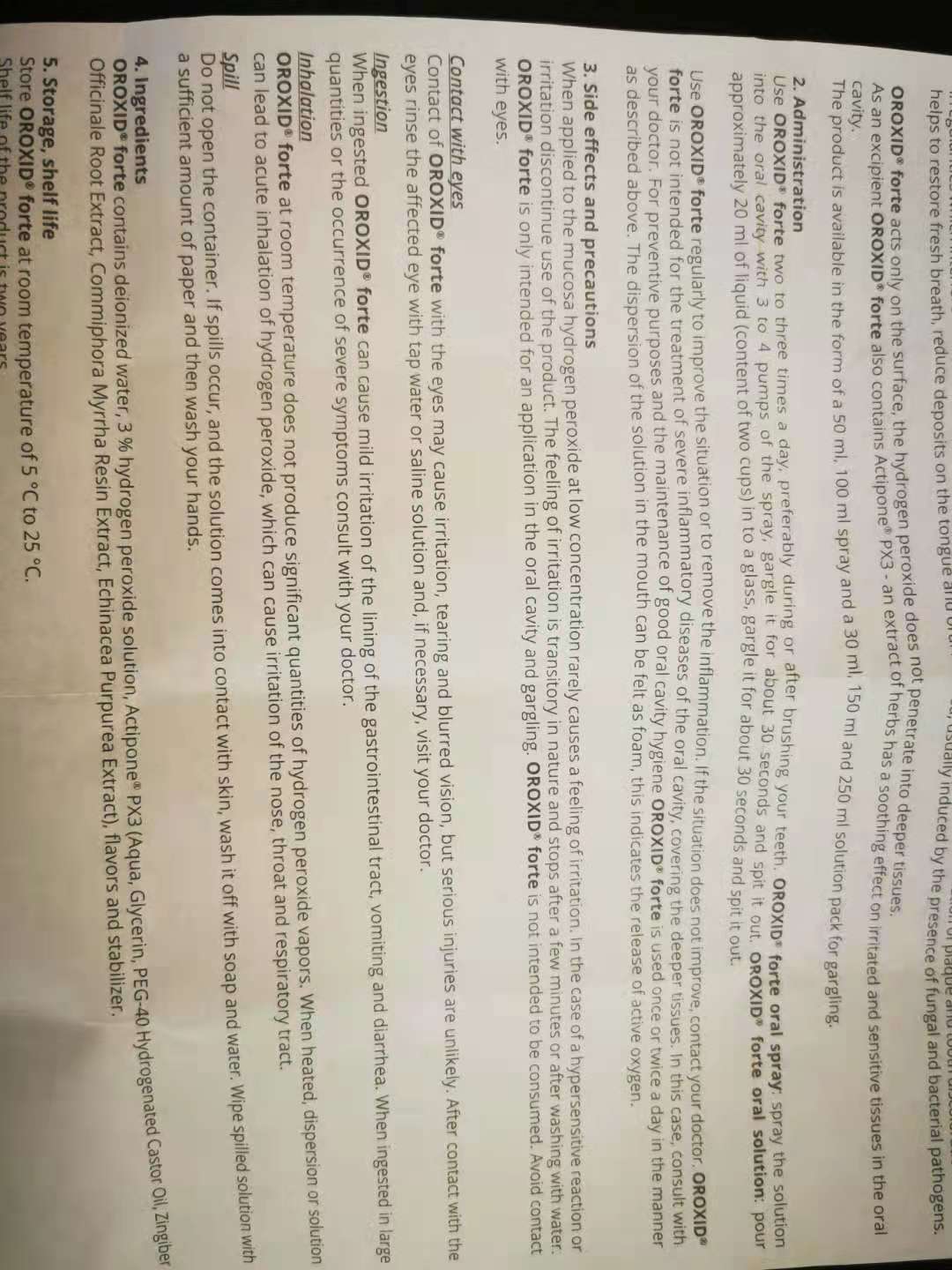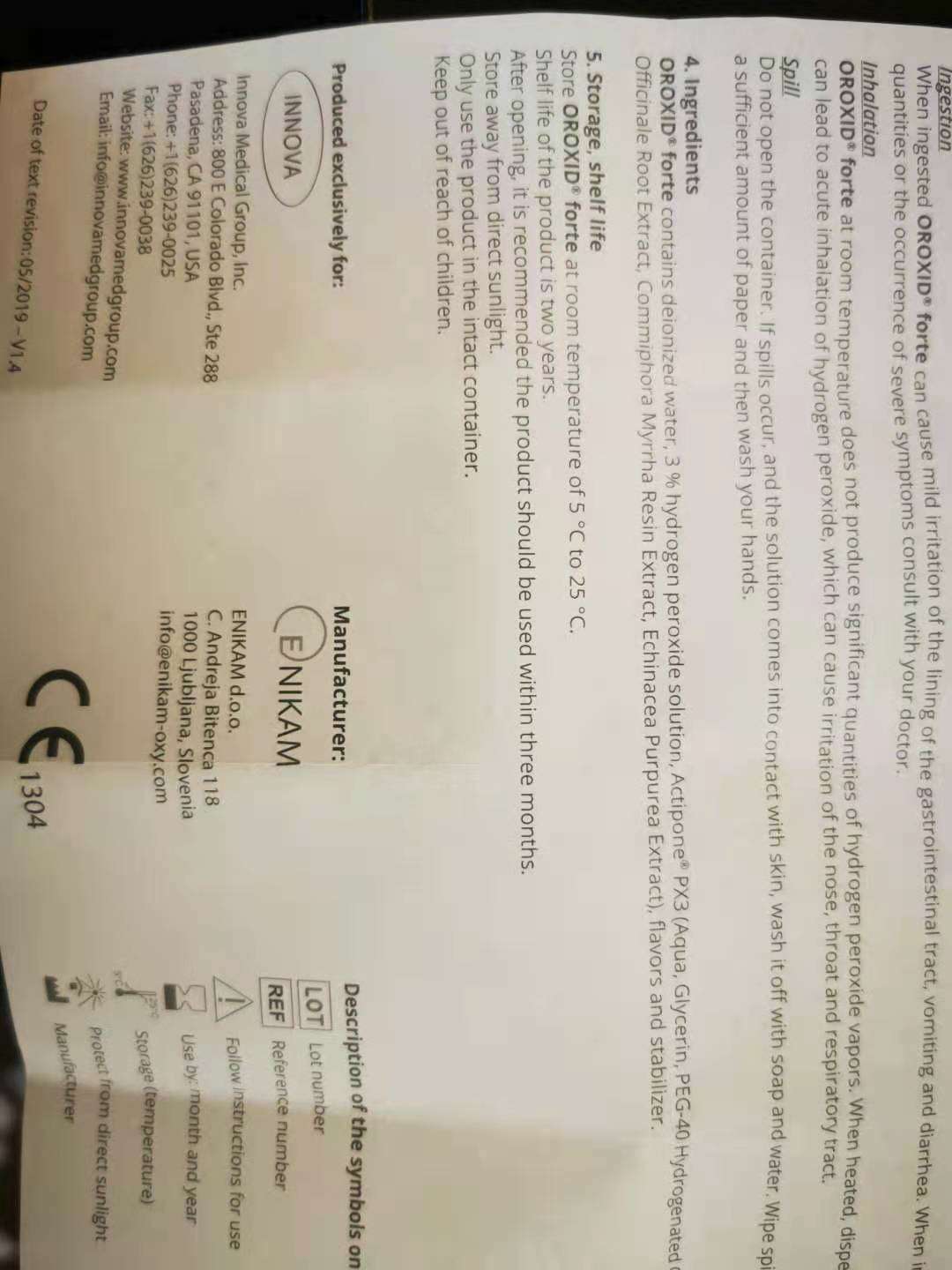 DRUG LABEL: OROXID Forte Oral Hygiene
NDC: 81794-800 | Form: SPRAY
Manufacturer: Innova Medical Group
Category: otc | Type: HUMAN OTC DRUG LABEL
Date: 20210712

ACTIVE INGREDIENTS: HYDROGEN PEROXIDE 2.94 mL/2.94 mL
INACTIVE INGREDIENTS: COMMIPHORA MYRRHA STEM BARK; GLYCERIN; WATER; GINGER; ECHINACEA PURPUREA; STEVIA EUPATORIA WHOLE; SPEARMINT; PEG-40 CASTOR OIL

Keep out of reach of children

Keep away from children

Storage and Handling

Store at Temperature of 5ºc to 25ºc

Protect from Direct sunlight

Warning

Avoid direct contact with eyes

Innovative Help With

Gingivits, Periodontitis

Inflammation of oral cavity

Bleeding and irritated gums

Intensive oral hygiene(Fixed dental braces, prosthesis, implants)

Reduction of deposit on the tongue

Prevention of dental plaque

Reduction of tooth stains

Restoration of fresh breath

How to use

Use OROXID Forte two to three times a day prederably during or after brushing your teech. Spray the solution into the oral cavity with 3 to 4 pressures of the spray, gargle for about 30 seconds and spit it out. Use OROXID forte reqularly, until the situation of elimincation of inflammation immproves.

Dosage Administrationt

3 to 4 pressure of the spray, two to three times a day

Active Ingredient

Hydrogen peroxide

Inactive ingredient

deionized water